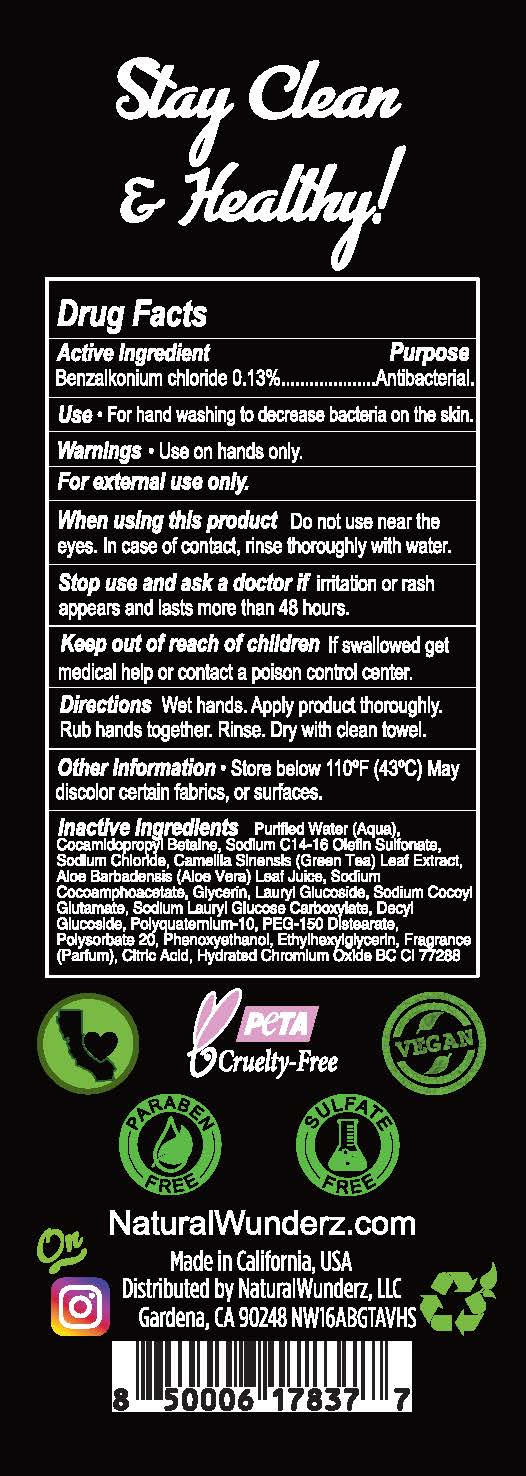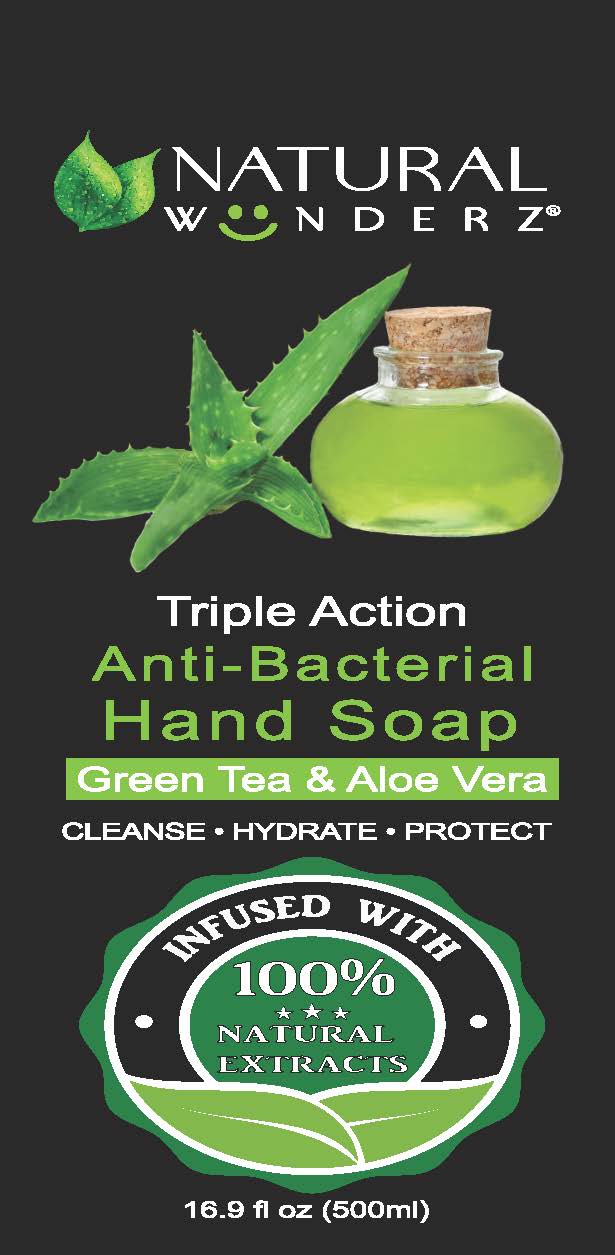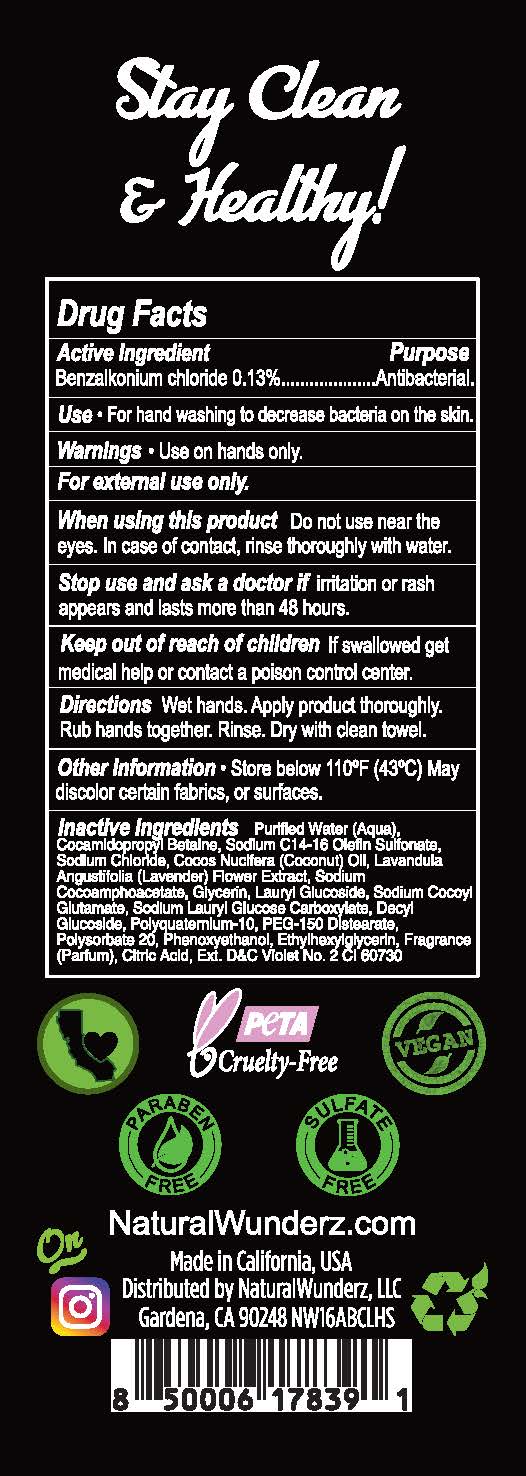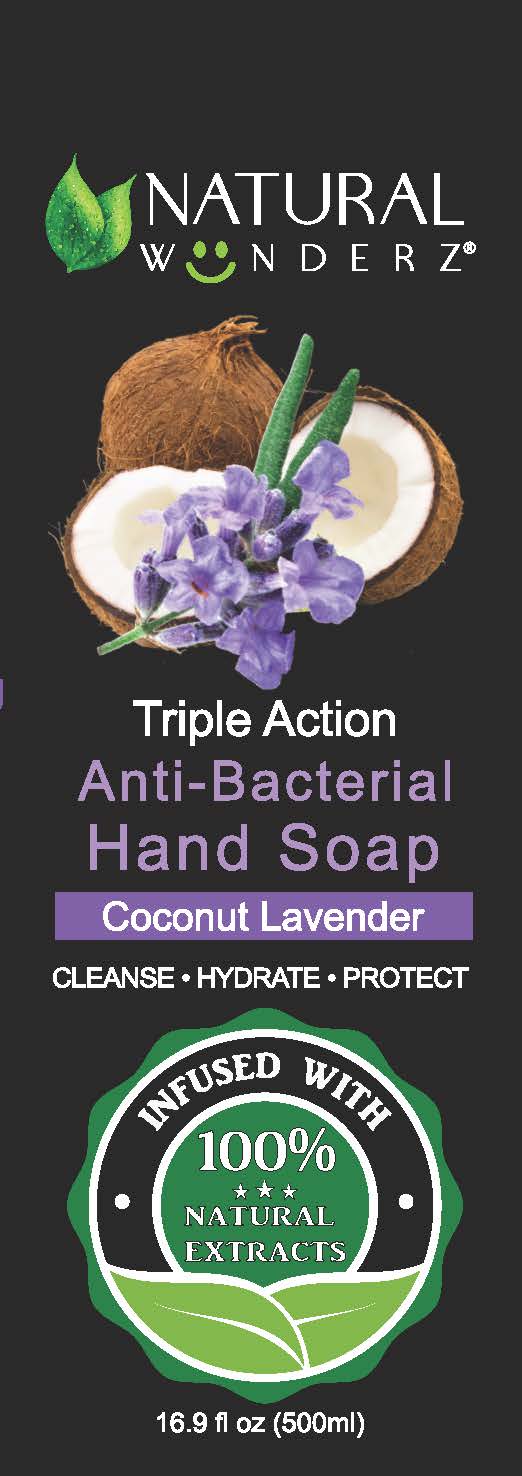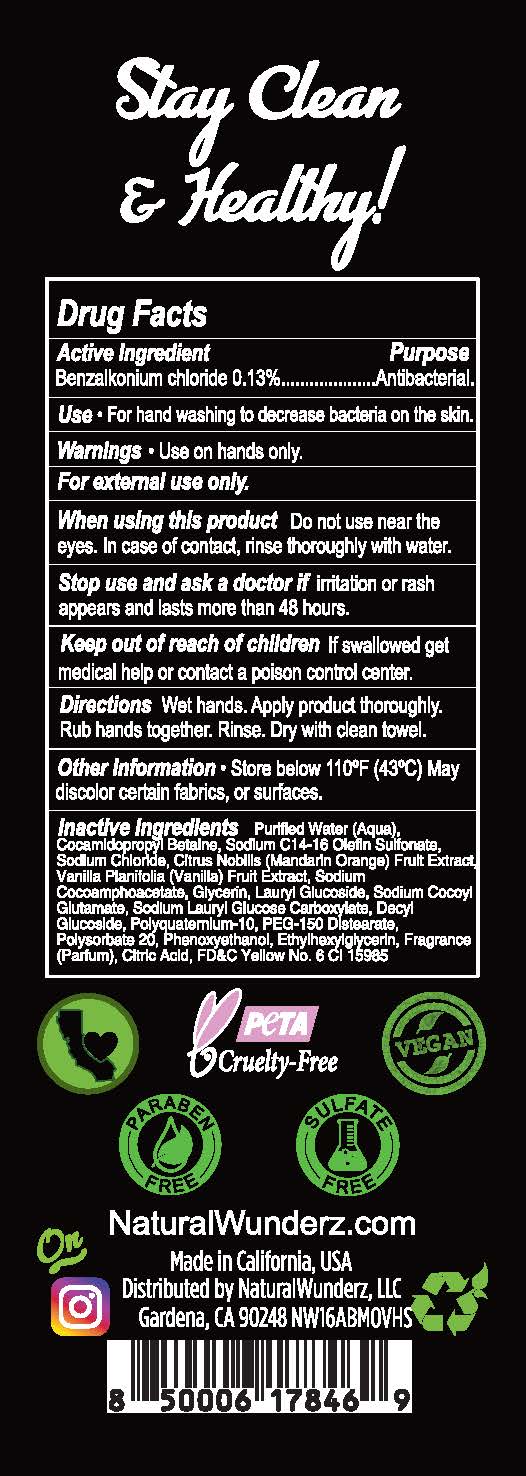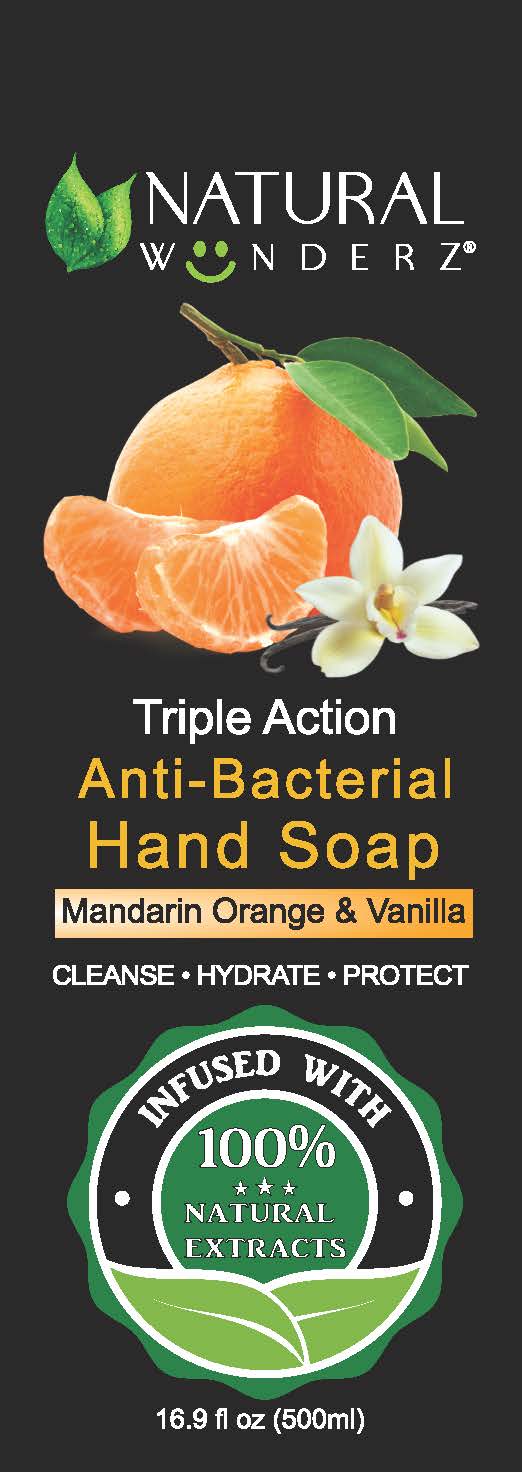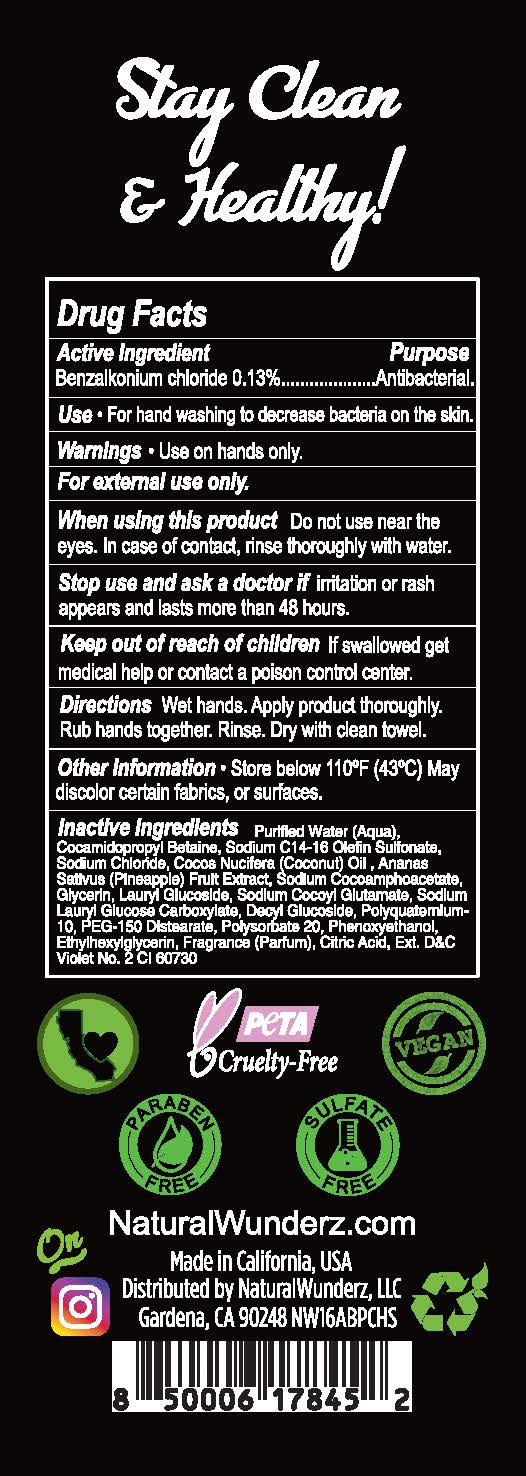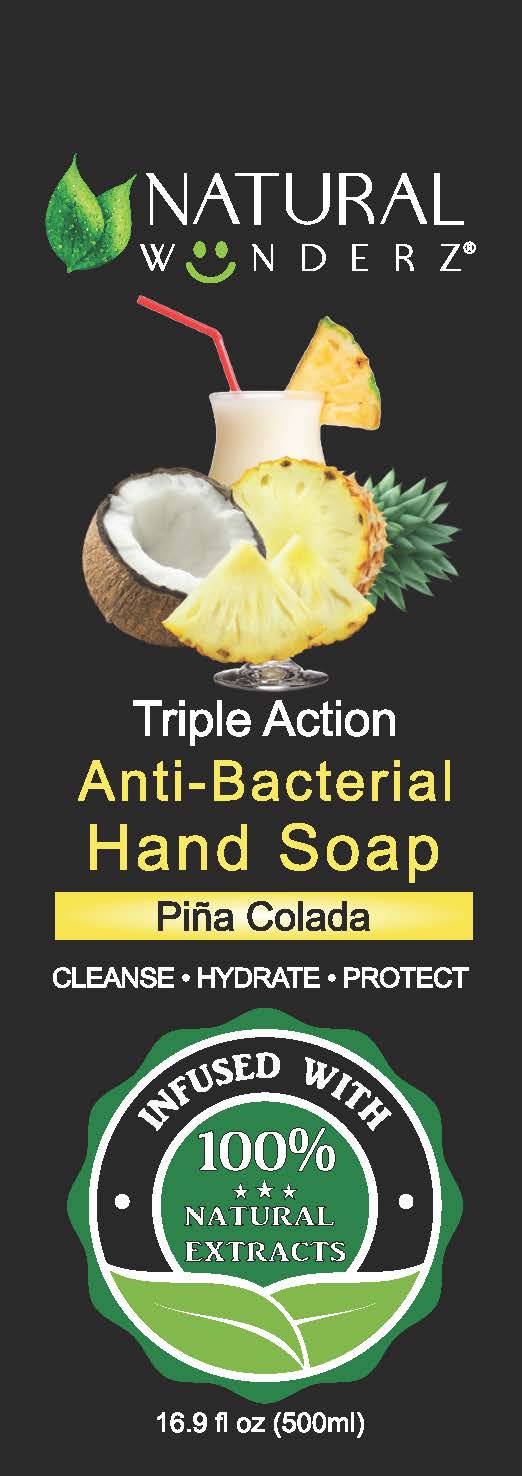 DRUG LABEL: Natural Wunderz Anti-Bacterial Hand
NDC: 79360-102 | Form: SOAP
Manufacturer: Natural Wunderz, LLC
Category: otc | Type: HUMAN OTC DRUG LABEL
Date: 20200804

ACTIVE INGREDIENTS: BENZALKONIUM CHLORIDE 0.13 g/100 mL
INACTIVE INGREDIENTS: WATER; COCAMIDOPROPYL BETAINE; SODIUM C14-16 OLEFIN SULFONATE; SODIUM CHLORIDE; GREEN TEA LEAF; ALOE VERA LEAF; SODIUM COCOAMPHOACETATE; GLYCERIN; LAURYL GLUCOSIDE; SODIUM COCOYL GLUTAMATE; SODIUM LAURYL GLYCOL CARBOXYLATE; DECYL GLUCOSIDE; POLYQUATERNIUM-10 (1000 MPA.S AT 2%); PEG-150 DISTEARATE; POLYSORBATE 20; PHENOXYETHANOL; ETHYLHEXYLGLYCERIN; ANHYDROUS CITRIC ACID; CHROMIUM HYDROXIDE GREEN; COCONUT OIL; LAVENDER OIL; EXT. D&C VIOLET NO. 2; BANANA; CITRUS NOBILIS; VANILLA PLANIFOLIA WHOLE; FD&C YELLOW NO. 6

NATURAL WUNDERZ TRIPLE ACTION ANTI-BACTERIAL HAND SOAP

ACTIVE INGREDIENT

BENZALKONIUM CHLORIDE 0.13%

PURPOSE

ANTIBACTERIAL

USE

FOR HAND WASKING TO DECREASE BACTERIA ON THE SKIN.

WARNINGS

USE ON HANDS ONLY.

For external use only.

When using this product Do not use near the eyes. In case of contact, rinse thoroughly with water.

Stop use and ask a doctor if irritation or rash appears and lasts for more than 48 hours.

Keep out of reach of children.

If swallowed, get medical help or contact a Poison Control Center right away.

Keep out of reach of children. If swallowed get medical help or contact a poison control center.

DIRECTIONS

Wet hands. Apply product thoroughly. Rub hands together. Rinse. Dry with clean towel.

INACTIVE INGREDIENTS

GREEN TEA AND ALOE VERA: Purified Water (Aqua), Cocamidopropyl Betaine, Sodium C14-16 Olefin Sulfonate, Sodium Chloride, Camelia Sinensis (Green Tea) Leaf Extract, Aloe Barbadensis (Aloe Vera) Leaf Juice, Sodium Cocoamphoacetate, Glycerin, Lauryl Glucoside, Sodium Cocoyl Glutamate, Sodium Lauryl Glucose Carboxylate, Decyl Glucoside, Polyquaternium-10, PEG-150 Distearate, Polysorbate 20, Phenoxyethanol, Ethylhexylglycerin, Fragrance (Parfum), Citric Acid, Hydrated Chromium Oxide BC CI 77288

COCONUT LAVENDER: Purified Water (Aqua), Cocamidopropyl Betaine, Sodium C14-16 Olefin Sulfonate, Sodium Chloride, Cocos Nucifera (Coconut) Oil, Lavandula Angustifolia (Lavender) Flower Extract, Sodium Cocoamphoacetate, Glycerin, Lauryl Glucoside, Sodium Cocoyl Glutamate, Sodium Lauryl Glucose Carboxylate, Decyl Glucoside, Polyquaternium-10, PEG-150 Distearate, Polysorbate 20, Phenoxyethanol, Ethylhexylglycerin, Fragrance (Parfum), Citric Acid, Ext. D&C Violet No. 2 CI 60730

PINA COLADA: Purified Water (Aqua), Cocamidopropyl Betaine, Sodium C14-16 Olefin Sulfonate, Sodium Chloride, Cocos Nucifera (Coconut) Oil, Ananas Sativus (Pineapple) Fruit Extract, Sodium Cocoamphoacetate, Glycerin, Lauryl Glucoside, Sodium Cocoyl Glutamate, Sodium Lauryl Glucose Carboxylate, Decyl Glucoside, Polyquaternium-10, PEG-150 Distearate, Polysorbate 20, Phenoxyethanol, Ethylhexylglycerin, Fragrance (Parfum), Citric Acid, Ext. D&C Violet No. 2 CI 60730

MANDARIN ORANGE AND VANILLA: Purified Water (Aqua), Cocamidopropyl Betaine, Sodium C14-16 Olefin Sulfonate, Sodium Chloride, Citrus Nobilis (Mandarin Orange) Fruit Extract, Vanilla Planifolia (Vanilla) Fruit Extract, Sodium Cocoamphoacetate, Glycerin, Lauryl Glucoside, Sodium Cocoyl Glutamate, Sodium Lauryl Glucose Carboxylate, Decyl Glucoside, Polyquaternium-10, PEG-150 Distearate, Polysorbate 20, Phenoxyethanol, Ethylhexylglycerin, Fragrance (Parfum), Citric Acid, FD&C Yellow No. 6 CI 15985

OTHER INFORMATION

Store below 110°F (43°C). May discolor certain fabrics, or surfaces.